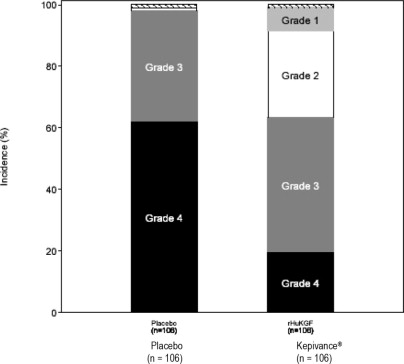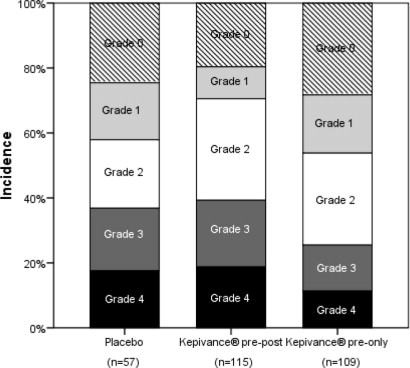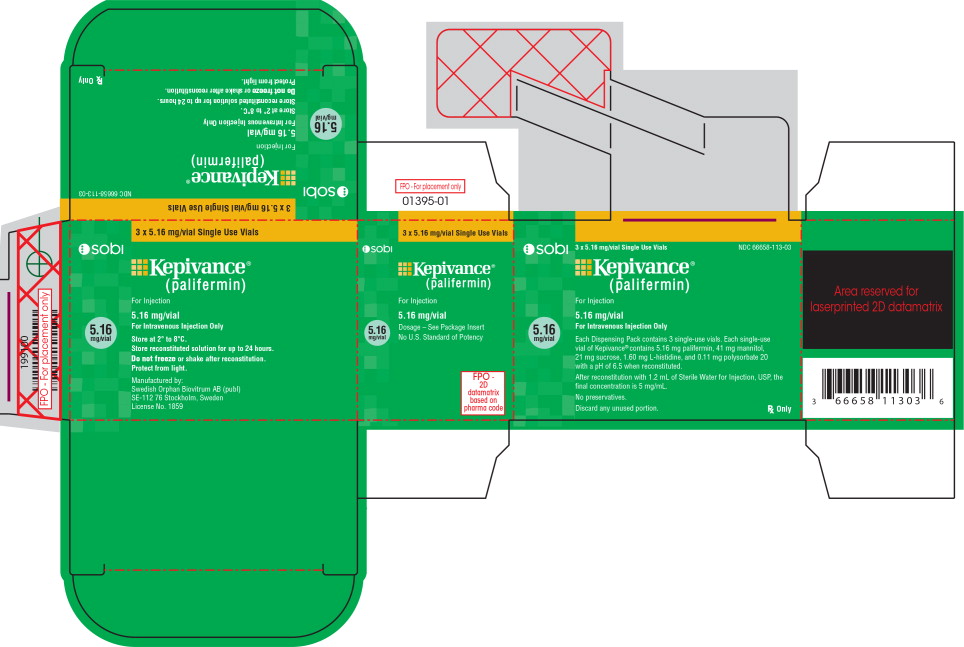 DRUG LABEL: KEPIVANCE
NDC: 66658-113 | Form: INJECTION, POWDER, LYOPHILIZED, FOR SOLUTION
Manufacturer: Swedish Orphan Biovitrum AB (publ)
Category: prescription | Type: HUMAN PRESCRIPTION DRUG LABEL
Date: 20251217

ACTIVE INGREDIENTS: PALIFERMIN 5.16 mg/1.2 mL
INACTIVE INGREDIENTS: MANNITOL 41 mg/1.2 mL; SUCROSE 21 mg/1.2 mL; HISTIDINE 1.6 mg/1.2 mL; POLYSORBATE 20 0.11 mg/1.2 mL

HIGHLIGHTS OF PRESCRIBING INFORMATION

These highlights do not include all the information needed to use Kepivance safely and effectively. See full prescribing information for KEPIVANCE.
KEPIVANCE®(palifermin) for injection, for intravenous use
Initial U.S. Approval: 2004

1 INDICATIONS AND USAGE

- Kepivance is a mucocutaneous epithelial human growth factor indicated to decrease the incidence and duration of severe oral mucositis in patients with hematologic malignancies receiving myelotoxic therapy in the setting of autologous hematopoietic stem cell support. Kepivance is indicated as supportive care for preparative regimens predicted to result in ≥ WHO Grade 3 mucositis in the majority of patients. (1.1)

Limitations of Use

- The safety and efficacy of Kepivance have not been established in patients with non-hematologic malignancies (1.2, 5.1)
- Kepivance was not effective in decreasing the incidence of severe mucositis in patients with hematologic malignancies receiving myelotoxic therapy in the setting of allogeneic hematopoietic stem cell support. (1.2, 14.3)
- Kepivance is not recommended for use with melphalan 200 mg/m^2as a conditioning regimen (14.2).

2 DOSAGE AND ADMINISTRATION

Administer as an intravenous bolus injection at a dose of 60 mcg/kg/day for 3 consecutive days before and 3 consecutive days after myelotoxic therapy for a total of 6 doses (2.1)

- Administer the first 3 doses prior to myelotoxic therapy with the third dose 24 to 48 hours before myelotoxic therapy (2.1)
- Administer the last 3 doses after myelotoxic therapy is complete with the first of these doses on the day of hematopoietic stem cell infusion after the infusion is completed, and at least 7 days after the most recent administration of Kepivance (2.1)

3 DOSAGE FORMS AND STRENGTHS

For injection: 5.16 mg lyophilized powder in single-dose vials (3)

4 CONTRAINDICATIONS

None

5 WARNINGS AND PRECAUTIONS

Potential for stimulation of tumor growth — Kepivance is not indicated for non-hematologic tumors. The effects of Kepivance on stimulation of keratinocyte growth factor (KGF) receptor-expressing, non-hematopoietic tumors in patients are not known (1, 5.1)

6 ADVERSE REACTIONS

Most common adverse reactions (incidence ≥20% and 5%≥placebo) are rash, fever, elevated serum amylase, pruritus, erythema, and edema (6)

To report SUSPECTED ADVERSE REACTIONS, contact Swedish Orphan Biovitrum at 1-866-773-5274 or FDA at 1-800-FDA-1088 orwww.fda.gov/medwatch.

7 DRUG INTERACTIONS

- Heparin increases systemic exposure; flush intravenous line between heparin and Kepivance. (7)
- Do not administer within 24 hours of myelotoxic chemotherapy. (7, 14)

8 USE IN SPECIFIC POPULATIONS

- Pregnancy: Based on animal data, may cause fetal harm (8.1)
- Lactation: Breastfeeding not recommended 8.2)

FULL PRESCRIBING INFORMATION

1 INDICATIONS AND USAGE

1.1 Indications

Kepivance is indicated to decrease the incidence and duration of severe oral mucositis in patients with hematologic malignancies receiving myelotoxic therapy in the setting of autologous hematopoietic stem cell support. Kepivance is indicated as supportive care for preparative regimens predicted to result in ≥ WHO Grade 3 mucositis in the majority of patients. Kepivance is a mucocutaneous epithelial human growth factor indicated to decrease the incidence and duration of severe oral mucositis in patients with hematologic malignancies receiving myelotoxic therapy in the setting of autologous hematopoietic stem cell support. Kepivance is indicated as supportive care for preparative regimens predicted to result in ≥ WHO Grade 3 mucositis in the majority of patients.

1.2 Limitations of Use

The safety and efficacy of Kepivance have not been established in patients with non-hematologic malignancies)]. The safety and efficacy of Kepivance have not been established in patients with non-hematologic malignancies [see Warnings and Precautions (5.1)].

Kepivance was not effective in decreasing the incidence of severe mucositis in patients with hematologic malignancies receiving myelotoxic therapy in the setting of allogeneic hematopoietic stem cell support. Kepivance was not effective in decreasing the incidence of severe mucositis in patients with hematologic malignancies receiving myelotoxic therapy in the setting of allogeneic hematopoietic stem cell support [See Clinical Studies (14.3)] .

Kepivance is not recommended for use with melphalan 200 mg/m as a conditioning regimen. Kepivance is not recommended for use with melphalan 200 mg/m^2as a conditioning regimen [See Clinical Studies (14.2)] .

2 DOSAGE AND ADMINISTRATION

2.1 Recommended Dosage Regimen

The recommended dose of Kepivance is 60 mcg/kg/day, administered as an intravenous bolus injection for 3 consecutive days before and 3 consecutive days after myelotoxic therapy, for a total of 6 doses. The recommended dose of Kepivance is 60 mcg/kg/day, administered as an intravenous bolus injection for 3 consecutive days before and 3 consecutive days after myelotoxic therapy, for a total of 6 doses.

Administer the first 3 doses prior to myelotoxic therapy. Administer the third dose 24 to 48 hours prior to beginning myelotoxic therapy Administer the first 3 doses prior to myelotoxic therapy. Administer the third dose 24 to 48 hours prior to beginning myelotoxic therapy [see Drug Interactions (7)].

Administer the last 3 doses after myelotoxic therapy is complete; administer the first of these doses on the day of hematopoietic stem cell infusion after the infusion is completed, and at least 7 days after the most recent administration of Kepivance [see Drug Interactions (7)].

2.2 Preparation and Administration

Preparation

Prepare the solution for infusion, using aseptic technique, as follows:

- Reconstitute Kepivance lyophilized powder with Sterile Water for Injection, USP (not supplied) by slowly injecting 1.2 mL of Sterile Water for Injection, USP to yield a final concentration of 5 mg/mL.
- Swirl the contents gently during dissolution. Do not shake or vigorously agitate the vial. Dissolution of Kepivance can take up to 3 minutes.
- Visually inspect the solution for discoloration and particulate matter before administration. The reconstituted solution should be clear and colorless. Do not administer Kepivance if discoloration or particulates are observed. Do not filter the reconstituted solution during preparation or administration. Do not freeze the reconstituted solution. Protect from light.

Administration

- Administer Kepivance by intravenous bolus injection. If heparin is used to maintain an intravenous line, rinse the line with saline prior to and after Kepivance administration [see Drug Interactions (7)].
- The reconstituted solution contains no preservatives and is intended for single use only. Discard any unused portion.
- Following reconstitution, it is recommended that the product be used immediately. If not used immediately, the reconstituted solution of Kepivance may be stored refrigerated in its carton at 2° to 8°C (36° to 46°F) for up to 24 hours.
- Prior to injection, allow Kepivance to reach room temperature for a maximum of 1 hour protected from light. Discard Kepivance left at room temperature for more than 1 hour.

3 DOSAGE FORMS AND STRENGTHS

For injection: 5.16 mg lyophilized powder in single-dose vials.

4 CONTRAINDICATIONS

None

5 WARNINGS AND PRECAUTIONS

5.1 Potential for Stimulation of Tumor Growth

The safety and efficacy of Kepivance have not been established in patients with non-hematologic malignancies. The effects of Kepivance on stimulation of KGF receptor-expressing, non-hematopoietic tumors in patients are not known. Kepivance has been shown to enhance the growth of human epithelial tumor cell lines in vitroand to increase the rate of tumor cell line growth in a human carcinoma xenograft model [see Clinical Pharmacology (12.1)].

6 ADVERSE REACTIONS

6.1 Clinical Trial Experience

Because clinical trials are conducted under widely varying conditions, adverse reaction rates observed in the clinical trials of a drug cannot be directly compared to rates in the clinical trials of another drug and may not reflect the rates observed in clinical practice.

The data described in Table 1and the discussion below reflect exposure to Kepivance in 409 patients with hematologic malignancies who were enrolled in 3 randomized, placebo-controlled clinical trials and a pharmacokinetic study. Patients received Kepivance either before, or before and after, regimens of myelotoxic chemotherapy, with or without total body irradiation (TBI), followed by hematopoietic stem cell support. Kepivance was administered in daily doses ranging from 5 to 80 mcg/kg/day. The total dose of Kepivance ranged from 15 to 480 mcg/kg with a median of 360 mcg/kg. The population had a median age of 48 years (range: 41 to 60 years), 62% were male and 83% were White with 7.4 % Black and 6.2 % Hispanic. Non Hodgkin's lymphoma (NHL) was the most common malignancy followed by Hodgkin's disease, multiple myeloma, and leukemia.

The most common adverse reactions attributed to Kepivance were skin toxicities (rash, erythema, edema, pruritus), oral toxicities (dysesthesia, tongue discoloration, tongue thickening, alteration of taste), pain, arthralgias, and dysesthesia. The median time to onset of cutaneous toxicity was 6 days following the first of 3 consecutive daily doses of Kepivance, with a median duration of 5 days. In patients receiving Kepivance, dysesthesia (including hyperesthesia, hypoesthesia, and paresthesia) was usually localized to the perioral region, whereas in patients receiving placebo dysesthesias were more likely to occur in extremities.

The most common serious adverse reaction attributed to Kepivance was skin rash, reported in less than 1% (3/409) of patients treated. Grade 3 skin rashes occurred in 3% of patients (9/409) receiving Kepivance and 2% (5/241) receiving placebo.

Table 1. Incidence of Adverse Reactions Occurring with a Between-Group Difference of ≥ 5%
BODY SYSTEM Adverse Reaction | Kepivance (n = 409) % | Placebo (n = 241) %
BODY AS A WHOLE
Edema | 28 | 21
Pain | 16 | 11
Fever | 39 | 34
GASTROINTESTINAL
Mouth/Tongue Thickness or Discoloration | 17 | 8
MUSCULOSKELETAL
Arthralgia | 10 | 5
SKIN AND APPENDAGES
Rash | 62 | 50
Pruritus | 35 | 24
Erythema | 32 | 22
SPECIAL SENSES
Taste Altered | 16 | 8
CENTRAL NERVOUS SYSTEM / PERIPHERAL NERVOUS SYSTEM
Dysesthesia – Hyperesthesia / hypoesthesia/ paresthesia | 12 | 7
METABOLIC
Elevated serum lipase
All grades | 28 | 23
Grade 3 and 4 | 11 | 5
Elevated serum amylase
All grades | 62 | 54
Grade 3 and 4 | 38 | 31

Cataracts:In a postmarketing safety study, the incidence of cataracts was numerically higher among patients receiving Kepivance than in the control population. (See 14 CLINICAL STUDIES).

Infections:In a randomized, double-blind, placebo-controlled post-approval study designed to determine the efficacy of Kepivance with a high-dose melphalan preparative regimen, the incidence of treatment-emergent infections was significantly greater in patients treated with Kepivance compared to placebo. A total of 281 patients were randomized to 3 arms: Kepivance before melphalan on days -6, -5, -4 and after melphalan on days 0, 1, and 2 (pre-post) (n=115); Kepivance before melphalan on days -6, -5, -4 (pre) (n=109); or placebo (n=57). The incidence of reported infections were pre-post - 50%; pre - 47%; and placebo - 25% [see Clinical Studies (14.2)] .

Laboratory Test Findings:Reversible elevations in serum lipase and amylase, which did not require treatment, were reported in 28% and 62% of patients receiving Kepivance and 23% and 54% of patients receiving placebo. In general, peak increases were observed during the period of cytotoxic therapy and returned to baseline by the day of hematopoietic stem cell infusion. Amylase was mainly salivary in origin.

6.2 Immunogenicity

As with all therapeutic proteins, there is a potential for immunogenicity. The clinical significance of antibodies to Kepivance is unknown but may include decreased activity and/or cross reactivity with other members of the FGF family of growth factors.

In clinical trials, serum samples from patients treated with Kepivance were tested for antibodies to Kepivance using an electrochemiluminescence-based binding assay. Twelve of 645 patients (2%) tested positive; none had evidence of neutralizing activity in a cell-based assay.

The incidence of antibody positivity is highly dependent on the specific assay and its sensitivity. Additionally, the observed incidence of antibody positivity in an assay may be influenced by several factors including sample handling, timing of sample collection, concomitant medications and underlying disease. For these reasons, comparison of the incidence of antibodies to Kepivance with the incidence of antibodies to other products may be misleading.

6.3 Postmarketing Experience

The following adverse reactions have been identified during postapproval use of Kepivance in the stem cell transplant setting. Because these reactions are reported voluntarily from a population of uncertain size, it is not always possible to reliably estimate their frequency or establish a causal relationship to drug exposure.

- Vaginal edema and erythema;
- Palmar-plantar Erythrodysaesthesia Syndrome (also known as “hand-foot syndrome”)

7 DRUG INTERACTIONS

In vitroand in vivodata showed that palifermin interacts with unfractionated as well as low molecular weight heparins with no noticeable effect on the pharmacodynamics of either drug. If heparin is used to maintain an intravenous line, rinse the line with saline prior to and after Kepivance administration [see Clinical Pharmacology (12.3)] .

Do not administer Kepivance within 24 hours before, during infusion of, or within 24 hours after administration of myelotoxic chemotherapy [see Dosage and Administration (2.1) and Clinical Studies (14)]. In a clinical trial, administration of Kepivance within 24 hours of chemotherapy resulted in increased severity and duration of oral mucositis.

8 USE IN SPECIFIC POPULATIONS

8.1 Pregnancy

Risk Summary

Based on findings in animal studies, Kepivance may cause fetal harm when administered to pregnant women. There are no data available on Kepivance use in pregnant women to inform a drug-associated risk of major birth defects and miscarriage or adverse maternal or fetal outcomes. In animal reproduction studies, intravenous administration of palifermin to pregnant rabbits and rats during the period of organogenesis resulted in embryo-fetal mortality and alterations to growth [see Data] .

The estimated background risk of major birth defects and miscarriage for the indicated populations is unknown. All pregnancies have a background risk of birth defect, loss, or other adverse outcomes. In the U.S. general population, the estimated background risk of major birth defects and miscarriage in clinically recognized pregnancies is 2-4% and 15-20%, respectively.

Data

Animal data

In embryo-fetal development studies, palifermin was administered intravenously to pregnant rabbits and rats during the perid of organogenesis. Doses were 5, 60, and 150 μg/kg/day in rabbits (gestation days 6-18) and 100, 300, and 1000 μg/kg/day in rats (gestation days 6 through 17). Increased post-implantation loss and decreased fetal body weights occurred along with maternal toxicity (clinical signs and reductions in body weight gain and food consumption) at doses of 150 μg/kg/day in rabbits and 1000 μg/kg/day in rats. Increased skeletal variations was noted in rats at 1000 μg/kg/day. Doses of 150 μg/kg/day in rabbits and 1000 μg/kg/day in rats are approximately 5-times (rabbits) and 35-times (rats) the exposure (AUC) in patients receiving the recommended dose of 60 μg/kg/day.

8.2 Lactation

Risk Summary

There are no data on the presence of Kepivance in human milk, the effect on the breastfed child, or the effect on milk production. Since many drugs are secreted into human milk, and because of the potential for serious adverse reactions in a nursing child, breastfeeding should be discontinued during treatment and for at least 2 weeks after the last dose.

8.3 Females and Males of Reproductive Potential

Infertility

Based on findings from animal studies, palifermin may impair fertility in females and males of reproductive potential [see Nonclinical Toxicology (13.1)] . The reversibility of the effects on fertility is unknown.

8.4 Pediatric Use

Information on the dosing and safety of Kepivance in the pediatric population is limited. However, use of Kepivance in pediatric patients ages 1 to 16 years is supported by evidence from adequate and well-controlled studies of Kepivance in adults and a phase 1 study that included 27 pediatric patients with acute leukemia undergoing hematopoietic stem cell transplant. Three age groups were studied: ages 1 to 2 (n=9), ages 3 to 11 (n=9), and ages 12 to 16 (n=9); 56% were male, 26% were Caucasian, 63% Hispanic; 81% ALL, 19% AML. The patients received high-dose cytotoxic therapy consisting of fractionated total body irradiation (TBI) (12 Gy total dose), high dose etoposide (1500 mg/m^2), and high dose cyclophosphamide (120 mg/kg) followed by allogeneic hematopoietic stem cell support. The dose intensity of this preparative regimen is comparable to the dose intensity of the Study 1 preparative regimen. See Clinical Studies [14.1]. Kepivance was administered as a daily intravenous injection for 3 consecutive days prior to initiation of cytotoxic therapy and for 3 consecutive days following infusion of hematopoietic stem cells. Three dose levels, 40, 60, and 80 mcg/kg/dose, were evaluated. There was no dose limiting toxicity identified at any dose level. Adverse events were similar to those reported in adult studies. The incidence of palifermin related adverse events was highest in the 80 μg/kg cohort. The overall incidence of WHO grade 3 and 4 oral mucositis was 10/27 (37%).

The pharmacokinetics of Kepivance was evaluated in the phase 1 study. Age (1 to 16 years) did not affect the pharmacokinetics of palifermin over the dose range (40 to 80 mcg/kg). Palifermin concentrations declined in the first 30 minutes after dosing. An increase in palifermin concentrations occurred at around 2 to 4 hours post-dose for some subjects, which was followed by a second, slow decline phase. A similar trend has been observed in adult patients. The mean half-life range was 2.6 to 5.6 hours in pediatric patients following the first 60 mcg/kg dose of Kepivance. No accumulation was observed following 3 consecutive doses of Kepivance. Palifermin exposure did not increase linearly with increasing doses. The first dose AUC0-inf(mean) of Kepivance 60 mcg/kg/day in adult patients (18 to 63 years) was 38.2 ng*hr/mL compared to 46.1 ng*hr/mL (range of means: 22.8 to 81.6) for pediatric patients (1 to 16 years). The mean clearance was 1730 mL/hr/kg for adults and 2481 mL/hr/kg (range of means: 1700 to 3460) in pediatric patients.

8.5 Geriatric Use

Clinical studies of Kepivance did not include sufficient numbers of subjects aged 65 years and older to determine whether they responded differently from younger subjects [see Clinical Pharmacology (12.3)].

11 DESCRIPTION

Kepivance (palifermin) is a truncated human KGF produced by recominant DNA technology in E coli. Kepivance is a water soluble, 140 amino acid protein with a molecular weight of 16.3 kilodaltons. It differs from endogenous human KGF in that the first 23 N terminal amino acids have been deleted to improve protein stability.

Kepivance is supplied as a sterile, white, preservative-free, lyophilized powder for intravenous injection after reconstitution with 1.2 mL of Sterile Water for Injection, USP. Reconstitution yields a clear, colorless solution of Kepivance (5 mg/mL) with a pH of 6.5. Each single-dose vial of Kepivance contains palifermin (5.16 mg),with L histidine (1.60 mg), mannitol (41 mg), polysorbate 20 (0.11 mg or 0.01% w/v), and sucrose (21 mg).

12 CLINICAL PHARMACOLOGY

12.1 Mechanism of Action

KGF is an endogenous protein in the fibroblast growth factor (FGF) family that binds to the KGF receptor. Binding of KGF to its receptor has been reported to result in proliferation, differentiation, and migration of epithelial cells. The KGF receptor, one of four receptors in the FGF family, has been reported to be present on epithelial cells in many tissues examined including the tongue, buccal mucosa, esophagus, stomach, intestine, salivary gland, lung, liver, pancreas, kidney, bladder, mammary gland, skin (hair follicles and sebaceous gland), and the lens of the eye. The KGF receptor has been reported to not be present on cells of the hematopoietic lineage. Endogenous KGF is produced by mesenchymal cells and is upregulated in response to epithelial tissue injury.

In mice and rats, Kepivance enhanced proliferation of epithelial cells (as measured by Ki67 immunohistochemical staining and BrDU uptake) and demonstrated an increase in tissue thickness of the tongue, buccal mucosa, and gastrointestinal tract. Kepivance has been studied in murine models of chemotherapy and radiation-induced gastrointestinal injury. In such models, administration of Kepivance prior to and/or after the cytotoxic insult improved survival and reduced weight loss compared to control animals.

Kepivance has been shown to enhance the growth of human epithelial tumor cell lines in vitroat concentrations ≥ 10 mcg/mL (> 15-fold higher than average therapeutic concentrations in humans). In nude mouse xenograft models, three consecutive daily treatments of Kepivance at doses of 1,500 and 4,000 mcg/kg (25- and 67-fold higher than the recommended human dose, respectively) repeated weekly for 4 to 6 weeks were associated with a dose-dependent increase in the growth rate of 1 of 7 KGF receptor-expressing human tumor cell lines.

12.2 Pharmacodynamics

Epithelial cell proliferation was assessed by Ki67 immunohistochemical staining in healthy subjects. A 3-fold or greater increase in Ki67 staining was observed in buccal biopsies from 3 of 6 healthy subjects given Kepivance at 40 mcg/kg/day intravenously for 3 days, when measured 24 hours after the third dose. Dose-dependent epithelial cell proliferation was observed in healthy subjects given single intravenous doses of 120 to 250 mcg/kg 48 hours post-dosing.

12.3 Pharmacokinetics

The pharmacokinetics of Kepivance were studied in healthy subjects and patients with hematologic malignancies. After single intravenous doses of 20 to 250 mcg/kg in healthy subjects and 60 mcg/kg in cancer patients, Kepivance concentrations declined over 95% in the first 30 minutes post-dose. A slight increase or plateau in concentration occurred at approximately 1 to 4 hours, followed by a terminal decline phase. Kepivance exhibited linear pharmacokinetics with extravascular distribution. In cancer patients compared with healthy subjects, after a 60 mcg/kg single dose of Kepivance the average total body clearance (CL) was 2- to 4-fold higher, and volume of distribution at steady state (Vss) was 2-fold higher. The elimination half-life was similar between healthy subjects and cancer patients (average 4.5 hours with a range of 3.3 to 5.7 hours). No accumulation of Kepivance occurred after 3 consecutive daily doses of 20 and 40 mcg/kg in healthy subjects or 60 mcg/kg in cancer patients. Age (1 to 16 years) did not affect the pharmacokinetics of palifermin over the dose range of 40 to 80 mcg/kg [see Use in Specific Populations (8.4)] .

Drug Interactions

Co-administration with Heparin

The potential pharmacokinetic interaction between palifermin and heparin was evaluated in a single-dose study in 27 healthy subjects receiving palifermin (60 mcg/kg) co-administered with and without therapeutic levels of unfractionated heparin. This co-administration resulted in a 5-fold increase in palifermin AUC and an 80% decrease in the mean CL. There was no significant effect of palifermin on heparin activity with respect to activated partial thromboplastin time (aPTT). A second study was conducted in 31 evaluable healthy subjects receiving palifermin (40 mcg/kg/day for 3 days) co-administered with and without therapeutic levels of unfractionated heparin. In this study, coadministration of heparin and palifermin resulted in a 425% increase in palifermin AUC and a 76.5, 73.1, and 38.8% decrease in palifermin CL, volume of distribution, and half-life, respectively. These changes in palifermin PK did not have a noticeable effect on Ki67 expression in buccal biopsies, used as a marker of epithelial cell proliferation.

Pharmacokinetics in Specific Populations

Renal Impairment

Results from a pharmacokinetics study in 24 subjects with varying degrees of renal impairment demonstrated that renal impairment has little or no influence on Kepivance pharmacokinetics.

Hepatic Impairment

The pharmacokinetic profile of patients with hepatic insufficiency has not been assessed.

Elderly

In a single-dose study, subjects received a 180-mcg/kg or 90-mcg/kg dose of palifermin administered by intravenous bolus injection. Subjects over the age of 65 (n=8) had an approximately 30% lower rate of CL on average than those 65 and younger (n=19). No dose adjustment is recommended for the geriatric population [see Use in Specific Populations (8.5)] .

13 NONCLINICAL TOXICOLOGY

13.1 Carcinogenesis, Mutagenesis, Impairment of Fertility

Palifermin was not carcinogenic in a 26-week study in rasH2 transgenic mice at intravenous doses of 0.1, 1, or 10 mg/kg/dose.

Palifermin was not genotoxic in the reverse mutation bacterial (Ames) test, cytogenic test, or rat micronucleus assay.

In a fertility and early embryonic development study, palifermin was administered intravenously to male and female rats at doses of 100, 300 or 1000 μg/kg/day. Males were dosed 28 days prior to mating through cohabitation and females were dosed 14 days prior to mating through gestation Day 7. Decreased epididymal sperm counts, and increased post-implantation losses were observed at doses ≥ 300 μg/kg/day (5 fold the recommended human dose, on a body weight basis). Increased pre-implantation loss and decreased fertility index, were observed at a palifermin dose of 1000 μg/kg/day.

14 CLINICAL STUDIES

14.1 Autologous transplantation preparative regimens that include total body irradiation

The safety and efficacy of Kepivance in decreasing the incidence and duration of severe oral mucositis in patients with hematologic malignancies (NHL, Hodgkin's disease, acute myeloid leukemia, acute lymphoblastic leukemia, chronic myeloid leukemia, chronic lymphocytic leukemia, or multiple myeloma) receiving myelotoxic therapy requiring hematopoietic stem cell support, were established in a randomized placebo-controlled clinical trial of 212 patients (Study 1) and a randomized, schedule-ranging, placebo-controlled clinical trial of 169 patients (Study 2).

In Study 1, patients received high-dose cytotoxic therapy consisting of fractionated total-body irradiation (TBI) (12 Gy total dose), high-dose etoposide (60 mg/kg), and high-dose cyclophosphamide (100 mg/kg) followed by hematopoietic stem cell support. Patients were randomized to receive either Kepivance (n = 106) or placebo (n = 106). Kepivance 60 mcg/kg was administered as a daily intravenous injection for 3 consecutive days prior to initiation of cytotoxic therapy and for 3 consecutive days following infusion of hematopoietic stem cells. The major efficacy outcome was the number of days during which patients experienced severe oral mucositis (Grade 3/4 on the WHO [World Health Organization] scale) [WHO Oral Mucositis Scale: Grade 1 = soreness/erythema; Grade 2 = erythema, ulcers, can eat solids; Grade 3 = ulcers, requires liquid diet only; Grade 4 = alimentation not possible.] . Other analyses included the incidence, duration, and severity of oral mucositis and the use of opioid analgesia. There was no evidence of a delay in time to hematopoietic recovery in patients who received Kepivance as compared to patients who received placebo. The results of Study 1 are presented in Table 2and Figure 1.

Table 2: Study 1 Efficacy Outcomes
Efficacy Variable | Kepivance (60 mcg/kg/day) (n = 106) | Placebo (n = 106)
Median (25th, 75thpercentile) Days of WHO Grade 3/4 Oral Mucositis* | 3 (0, 6) | 9 (6, 13)
Incidence of WHO Grade 3/4 Oral Mucositis | 63% (67/106) | 98% (104/106)
Median (25th, 75thpercentile) Days of WHO Grade 3/4 Oral Mucositis in Affected Patients | 6 (3, 8) (n = 67) | 9 (6, 13) (n = 104)
Incidence of WHO Grade 4 Oral Mucositis | 20% | 62%
Median (25th, 75thpercentile) Cumulative Opiod Dose (morphine mg equivalents) | 212 (3, 558) | 535 (269, 1429)
* P < 0.001 compared to placebo, using Generalized Cochran-Mantel-Haenszel (CMH) test stratified for study center.

Figure 1: Study 1 Incidence of Oral Mucositis by Maximum Grade WHO Oral Mucositis Scale

Study 2 was a randomized, multi-center, placebo-controlledtrial comparing varying schedules of Kepivance. All patients received high-dose cytotoxic therapy consisting of fractionated TBI (12cGy total dose), high-dose etoposide (60 mg/kg), and high-dose cyclophosphamide (75-100 mg/kg) followed by hematopoietic stem cell support. The results for Study 1 were supported by results observed in the subset of patients in Study 2 who received the same dose and schedule of Kepivance administered in Study 1. One arm of Study 2 that included patients who received Kepivance for 3 consecutive days prior to initiation of cytotoxic therapy, a dose given on the last day of TBI prior to etoposide, and for 3 consecutive days following infusion of hematopoietic stem cells was prematurely closed by the Safety Committee for lack of efficacy and a trend towards increased severity and duration of oral mucositis as compared to placebo-treated patients. The Safety Committee attributed the safety finding to Kepivance having been administered within 24 hours of chemotherapy, which resulted in an increased sensitivity of the rapidly dividing epithelial cells in the immediate post-chemotherapy period [see Dosage and Administration (2.1) and Drug Interactions (7)] .

14.2 Lack of Efficacy: Autologous transplantation preparative regimen using high dose melphalan

In a post approval study, Study 3, designed to determine the efficacy of Kepivance with a high dose melphalan preparative regimen, patients with multiple myeloma were evaluated in a multicenter, randomized, double-blind, placebo-controlled trial. The conditioning regimen was melphalan (200 mg/m^2) on day -2 followed by autologous hematopoietic stem cell support. A total of 281 patients were randomized to 3 arms: Kepivance before melphalan on days -6, -5, -4 and after melphalan on days 0, 1, and 2 (pre-post) (n=115); Kepivance before melphalan on days -6, -5, -4 (pre) (n=109); or placebo (n=57).

The main outcome of the study was maximum severity of WHO oral mucositis. The median age of enrolled patients was 57 years (range 32-69), and 55% were male. The results are presented in Figure 2. The prespecified primary analysis was a comparison between the Kepivance pre-post and pre arms to placebo. The incidence of WHO Grade 3 and 4 in the Kepivance pre-post arm was 38%, compared to 37% in the placebo arm. There were no significant differences between either of the Kepivance regimens and the placebo arm in the incidence of severe oral mucositis.

Figure 2: Incidence of Oral Mucositis by Maximum Grade WHO Oral Mucositis Scale in High Dose Melphalan Study

A subset of subjects enrolled in the multiple myeloma study were included in an evaluation for the risk of cataract development in patients receiving Kepivance treatment. Ophthalmologic examinations were performed on 101 patients enrolled in a double-blind, randomized, placebo-controlled study of two different schedules of Kepivance (pre and post chemotherapy and pre chemotherapy only) for reduction in severity of oral mucositis in subjects with multiple myeloma receiving high dose melphalan followed by autologous peripheral blood stem cell transplantation. For the primary cataract endpoint of incidence of cataract development or cataract progression at Month 12, there was a greater proportion of subjects that experienced cataract development in the Kepivance group: 48% (25/52) compared with the placebo group: 29% (4/14) (difference of 17 [95% CI: -11, 46]) [see Adverse Reactions (6.1)] .

14.3 Lack of Efficacy: Allogeneic Transplantation

In a post approval study, designed to determine the efficacy of Kepivance in decreasing the incidence of severe acute graft versus host disease (aGVHD) in patients with hematologic malignancies undergoing allogeneic transplantation, the incidence, duration and severity of oral mucositis was also measured. Multiple conditioning regimens were used. Patients were randomized to placebo (n=78) or to Kepivance (n=77) 60 micrograms/kg for 3 doses prior to the conditioning regimen and 180 micrograms/kg at least 24 hours from the last dose of chemotherapy and at least 24 hours before the first dose of post transplant methotrexate. There was no difference in the incidence of severe aGVHD Kepivance (16%) compared to placebo (17%). In addition to the lack of efficacy in preventing severe aGVHD, the incidence of WHO grade 3 and 4 mucositis was nominally higher in patients treated with Kepivance (81%) compared to placebo (73%).

16 HOW SUPPLIED/STORAGE AND HANDLING

Kepivance is supplied as a lyophilized powder in single-dose vials containing 5.16 mg of palifermin.

Kepivance vials are supplied in:

- a dispensing pack containing 3 vials (NDC 66658-113-03)

Store Kepivance vials in the dispensing pack in its carton refrigerated at 2° to 8°C (36° to 46°F) until time of use. Protect from light.

17 PATIENT COUNSELING INFORMATION

Advise patients to report the following to healthcare providers:

- Rashes and reddening of skin [see Adverse Reactions (6.1)]
- Itchiness [see Adverse Reactions (6.1)]
- Swelling of tongue [see Adverse Reactions (6.1)]
- Changes in mouth and tongue sensation [see Adverse Reactions (6.1)]
- Alteration in taste [see Adverse Reactions (6.1)]

Inform patients

- That the safety and efficacy of Kepivance have not been established in patients with non-hematologic malignancies [see Indications and Usage (1) and Warnings and Precautions (5.1)]
- Of the evidence of tumor growth and stimulation in cell culture and in animal models of non-hematopoietic human tumors [see Warnings and Precautions (5.1) and Clinical Pharmacology (12.1)]

sobi
SWEDISH ORPHAN BIOVITRUM
Manufactured by :
Swedish Orphan Biovitrum AB (publ)
SE-112 76 Stockholm, Sweden
U.S. License No. 1859

© Swedish Orphan Biovitrum AB (publ). All rights reserved.

PACKAGE LABEL

Principal Display Panel – 3 Pack 5.16 mg/1.2 mL Carton Label

sobi

3 x 5.16 mg/vial Single Use Vials

NDC 66658-113-03

Kepivance®
(palifermin)

For Injection

5.16 mg/vial

For Intravenous Injection Only

Each Dispensing Pack contains 3 single-use vials. Each single-use
vial of Kepivance® contains 5.16 mg palifermin, 41 mg mannitol,
21 mg sucrose, 1.60 mg L-histidine, and 0.11 mg polysorbate 20
with a pH of 6.5 when reconstituted.

After reconstitution with 1.2 mL of Sterile Water for Injection, USP, the
final concentration is 5 mg/mL.

No preservatives.

Discard any unused portion.

Rx Only